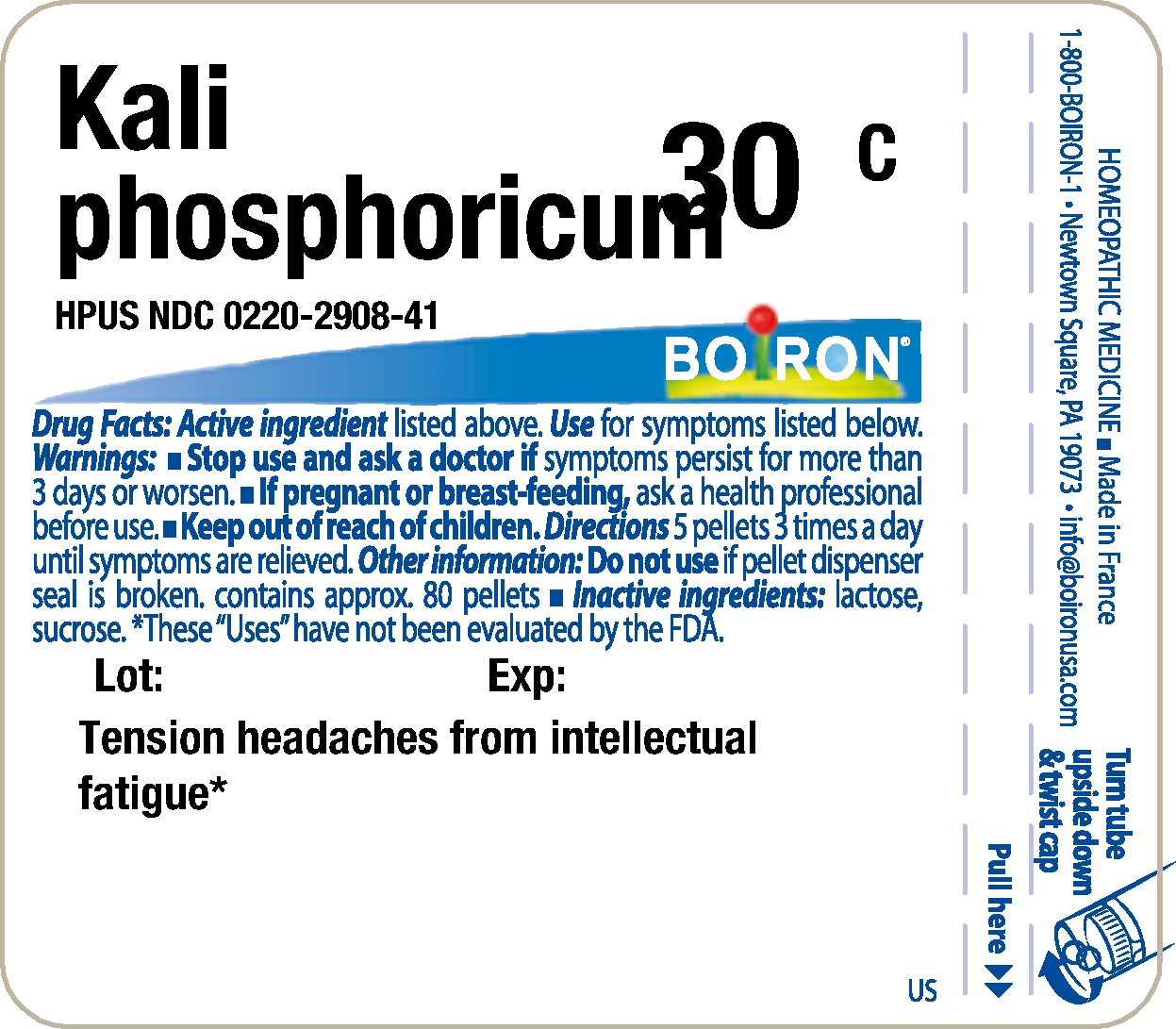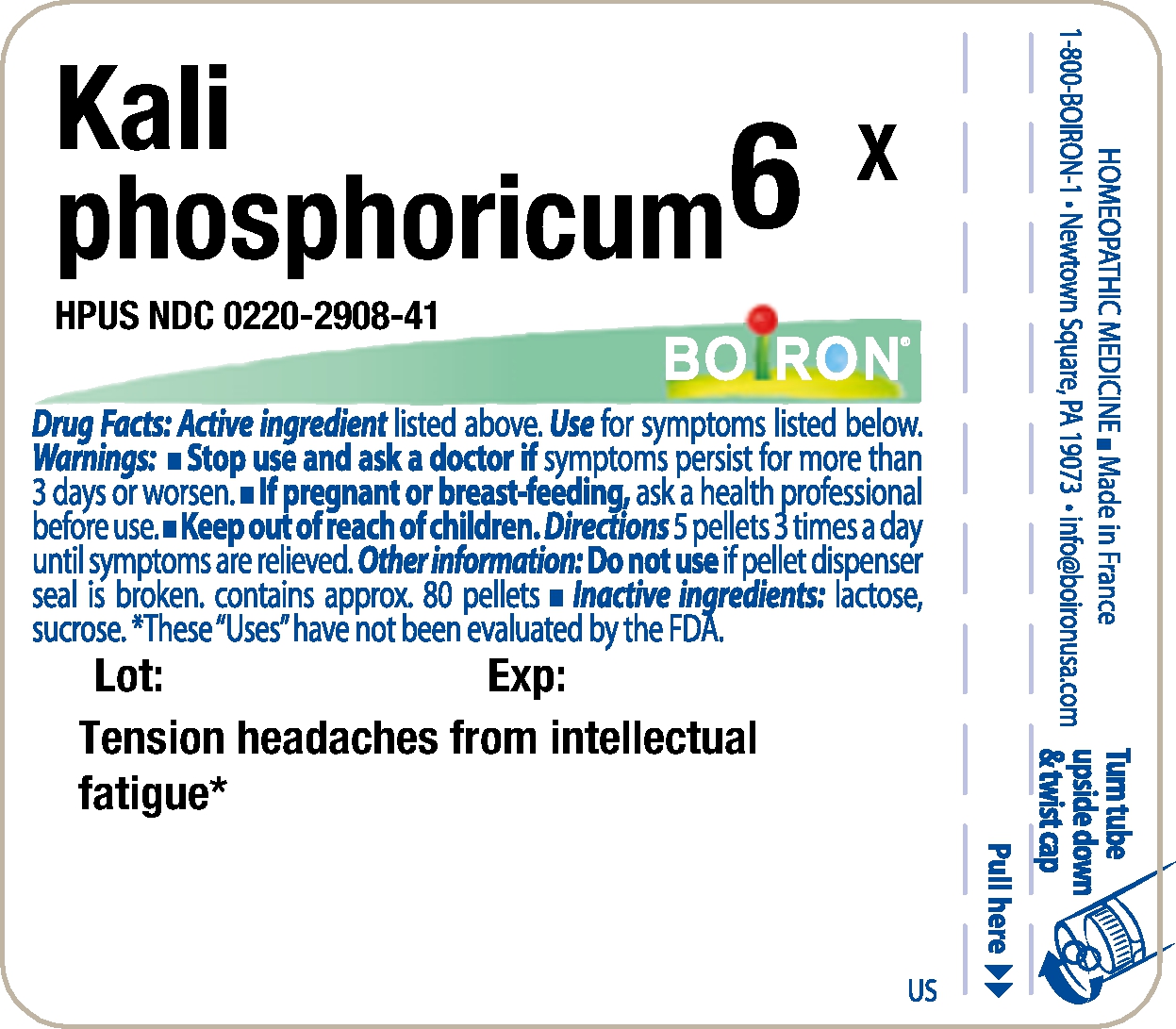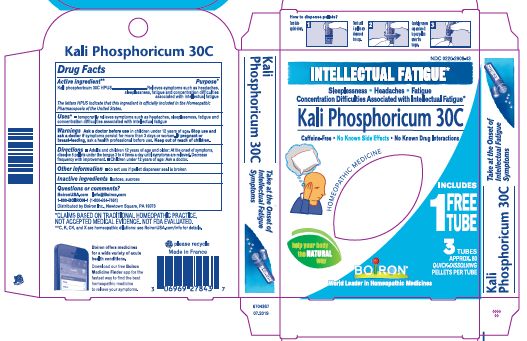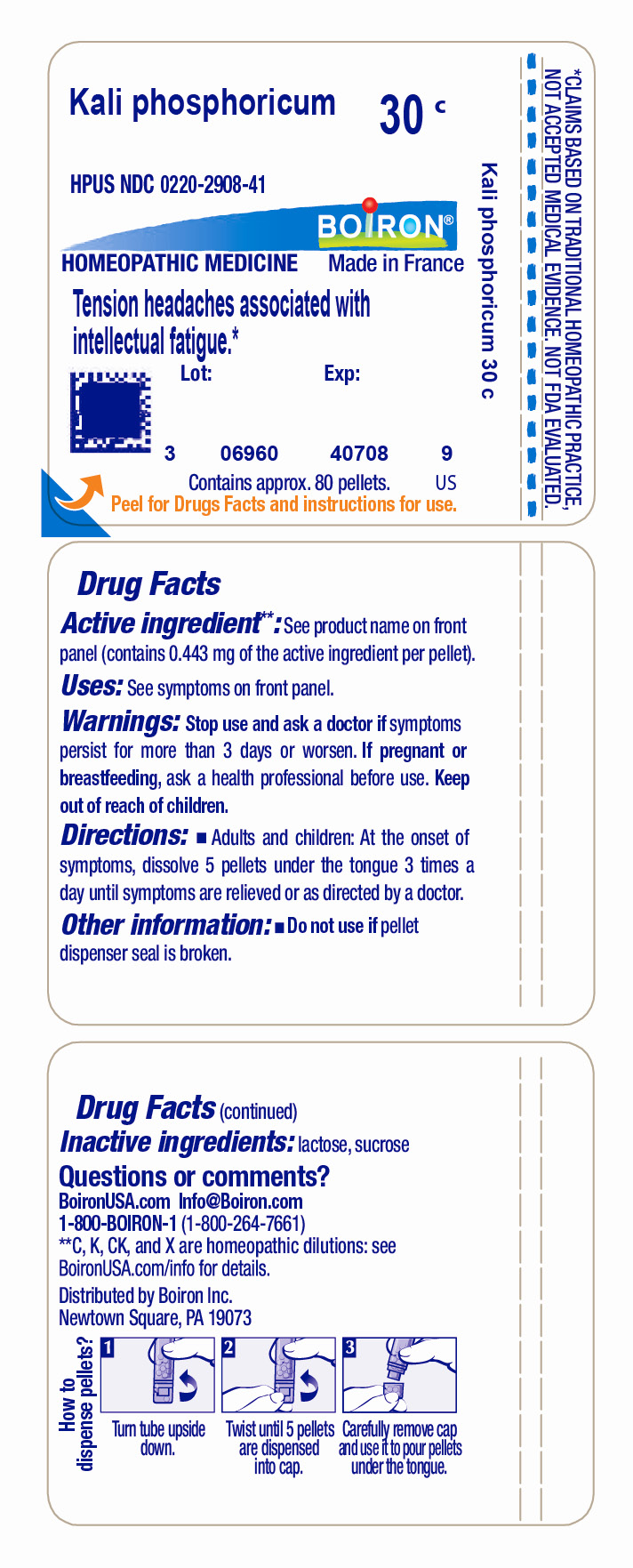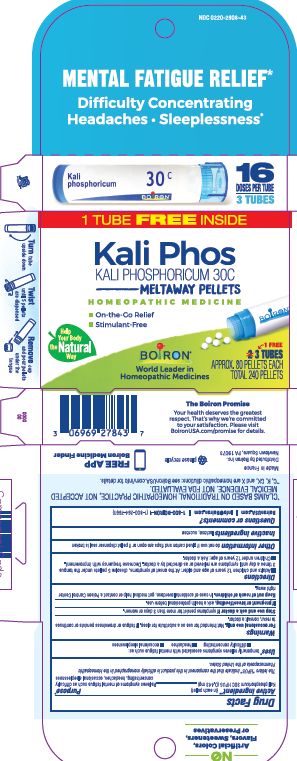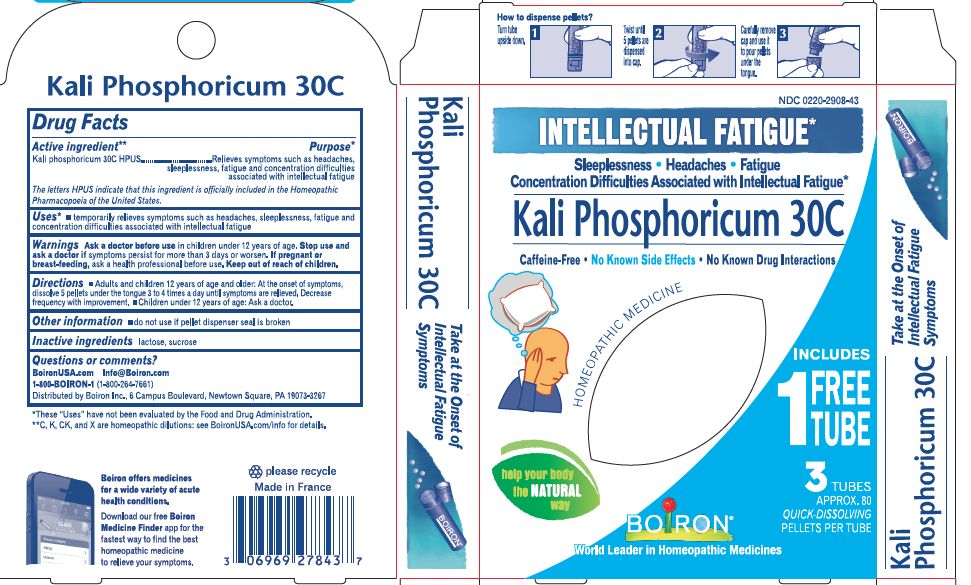 DRUG LABEL: Kali phosphoricum
NDC: 0220-2908 | Form: PELLET
Manufacturer: Laboratoires Boiron
Category: homeopathic | Type: HUMAN OTC DRUG LABEL
Date: 20230309

ACTIVE INGREDIENTS: POTASSIUM PHOSPHATE, DIBASIC 6 [hp_X]/1 1
INACTIVE INGREDIENTS: SUCROSE; LACTOSE

Kali phosphoricum

Active Ingredients

Kali phosphoricum HPUS (0.443 mg)** (in each pellet)

The letters "HPUS" indicate that the components in this product are officially monographed in the Homeopathic Pharmacopoeia of the United States.

PURPOSE

Relieves symptoms of mental fatigue such as difficulty concentrating, headaches, occasional sleeplessness*

INDICATIONS AND USAGE

*temporarily relieves symptoms associated with mental fatigue such as: difficulty concentrating, headaches, occasional sleeplessness

WARNINGS

For occasional use only. Not intended for use as a substitute for sleep. If fatigue or drowsiness persists or continues to recur, consult a doctor.

Stop use and ask a doctor if

symptoms persist for more than 3 days or worsen.

If pregnant or breast-feeding,

ask a health professional before use.

Keep out of reach of children. In case of accidental overdose, get medical help or contact a Poison Control Center right away.

Directions

Adults and children 12 years of age and doctor: At the onset of symptoms, dissolve 5 pellets under the tongue 3 times a day until symptoms are relieved or as directed by a doctor. Decrease frequency with improvement.

Children under 12 years of age: Ask a doctor.

Inactive ingredients

lactose, sucrose

QUESTIONS

BoironUSA.com

Info@boiron.com

1-800-BOIRON-1

1-800-264-7661

Distributed by Boiron, Inc.

Newtown Square, PA 19073-3267

Box:

Do not use if glued carton and flaps are open or if pellet dispenser seal is broken.

3 Tubes Approx. 80 Pellets Each Total 240 Pellets 16 Doses per tube 3 tubes

Difficulty Concentrating Headaches Sleeplessness*

Mental Fatigue Relief*

On-the-go relief

Stimulant-Free

Turn tube upside down. Twist until 5 pellets are dispensed. Remove cap and pour pellets under the tongue.

*CLAIMS BASED ON TRADITIONAL HOMEOPATHIC PRACTICE, NOT ACCEPTED MEDICAL EVIDENCE. NOT FDA EVALUATED.
*C,K,CK, and X are homeopathic dilutions: see BoironUSA.com/info for details.

Tube:

Do not use if pellet dispenser seal is broken.

Contains approx 80 pellets.
How to dispense pellets? Turn tube upside down. Twist until 5 pellets are dispensed into cap. Carefully remove the cap and use it to pour pellets under the tongue.
*CLAIMS BASED ON TRADITIONAL HOMEOPATHIC PRACTICE NOT ACCEPTED MEDICAL EVIDENCE. NOT FDA EVALUATED.
*C,K,CK, and X are homeopathic dilutions: see BoironUSA.com/info for details.